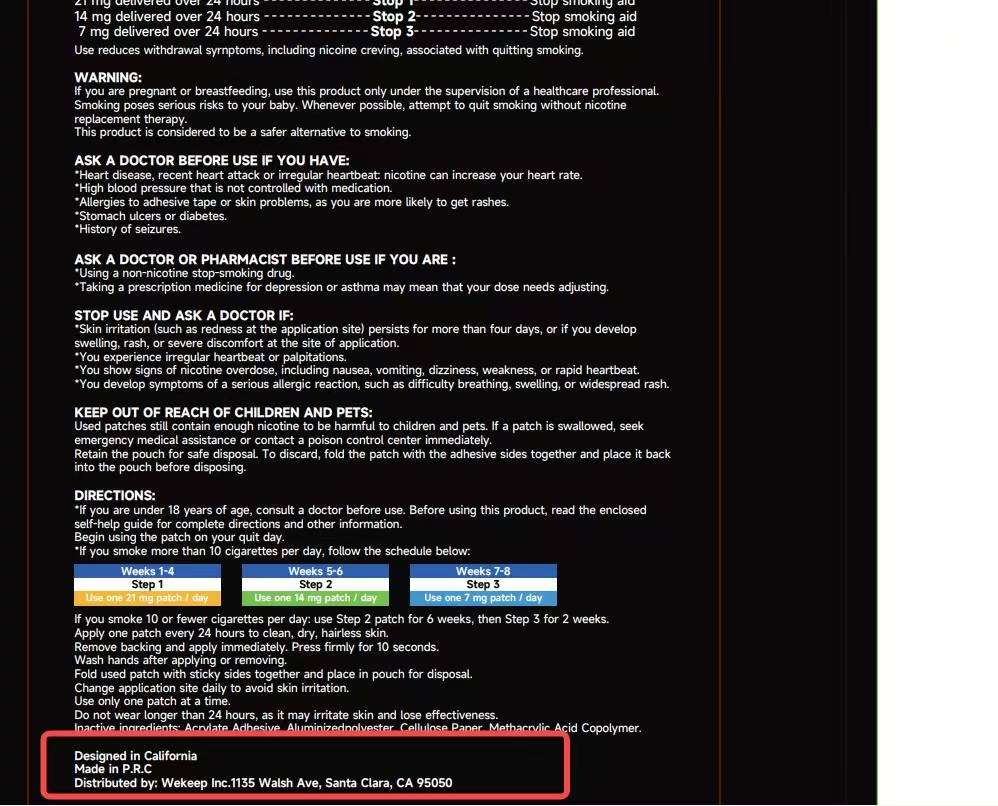 DRUG LABEL: Choppie Nicotine
NDC: 87076-3691 | Form: PATCH
Manufacturer: Shenzhen Yadifei Trading Co., Ltd.
Category: homeopathic | Type: HUMAN OTC DRUG LABEL
Date: 20250830

ACTIVE INGREDIENTS: NICOTINE 30 g/100 g
INACTIVE INGREDIENTS: PEPPERMINT OIL; CLOVE OIL; STAR ANISE OIL; GINGER OIL; SWEET MARJORAM OIL

ACTIVE INGREDIENT

Nicotine

PURPOSE

It is used for smokers to quit smoking

KEEP OUT OF REACH OF CHILDREN AND PETS

INDICATIONS AND USAGE

Apply one patch every 24 hours to clean,dry,hairless skin.Remove backing and apply immediately.Press firmly for 10 seconds.

Wash hands after applying or removing.Fold used patch with sticky sides together and place in pouch for disposal.Change application site daily to avoid skin irritation.

WARNINGS

if you are pregnant or breastfeeding,use this product only under the supervision of a healthcare professional,Smoking poses serious risks to your baby.

INACTIVE INGREDIENT

Clove Essential Oil,Star Anise Essential Oil,Sweet Orange Essential Oil,Peppermint Essential Oil,Ginger Essential Oil and Sweet Marjoram Essential Oil.

DOSAGE AND ADMINISTRATION

Use one 21 mg Patch/day

Use one 14 mg Patch/day

Use one 7 mg Patch/day